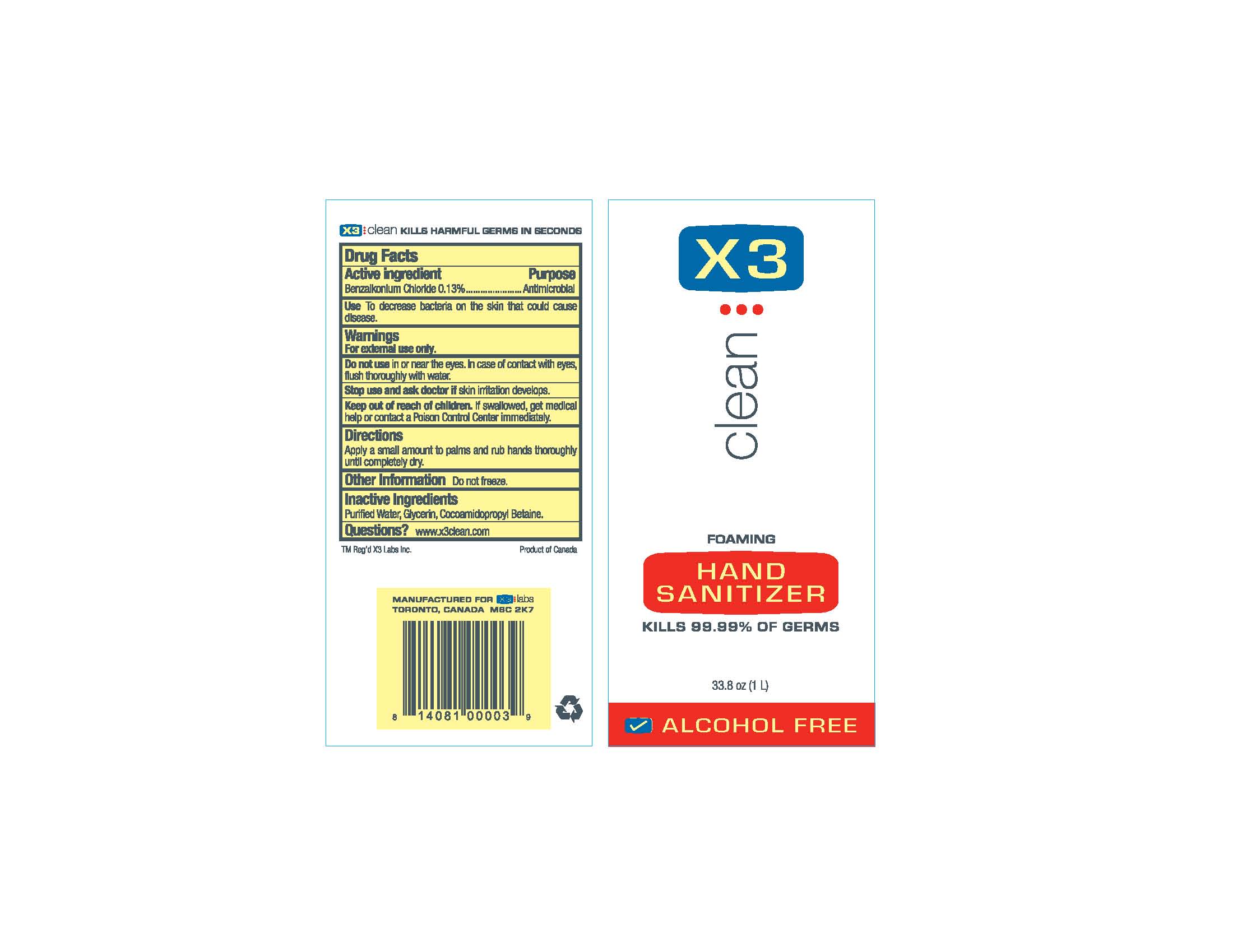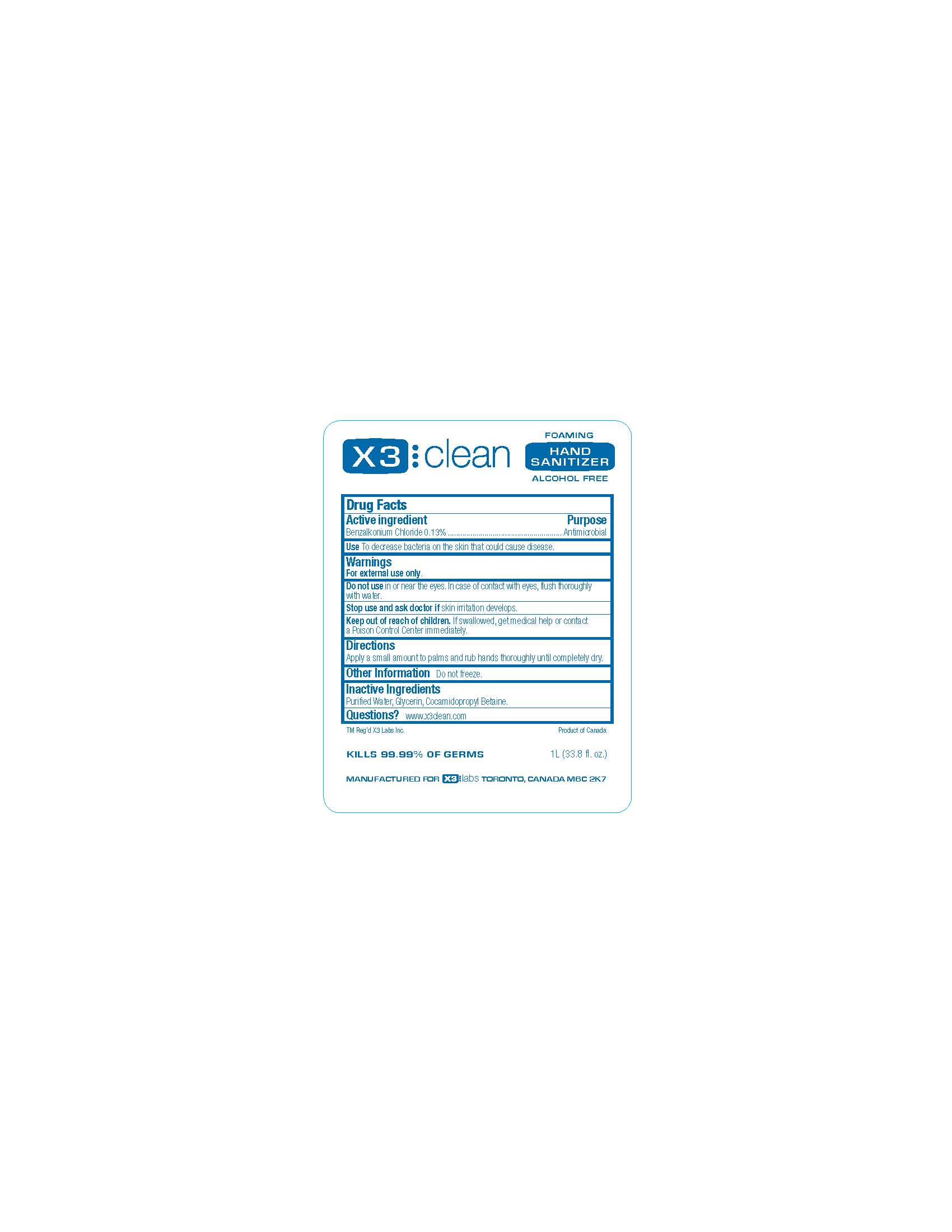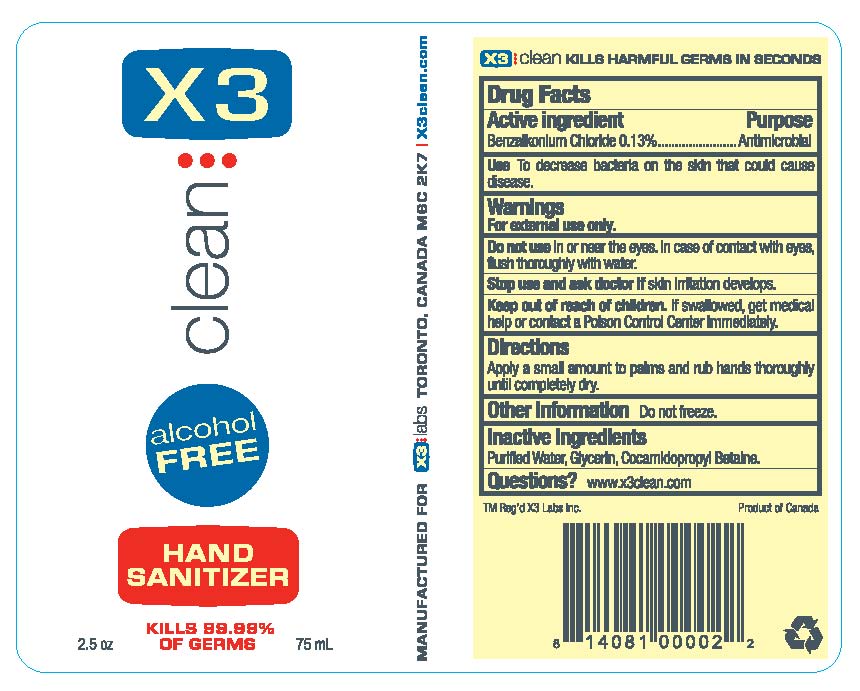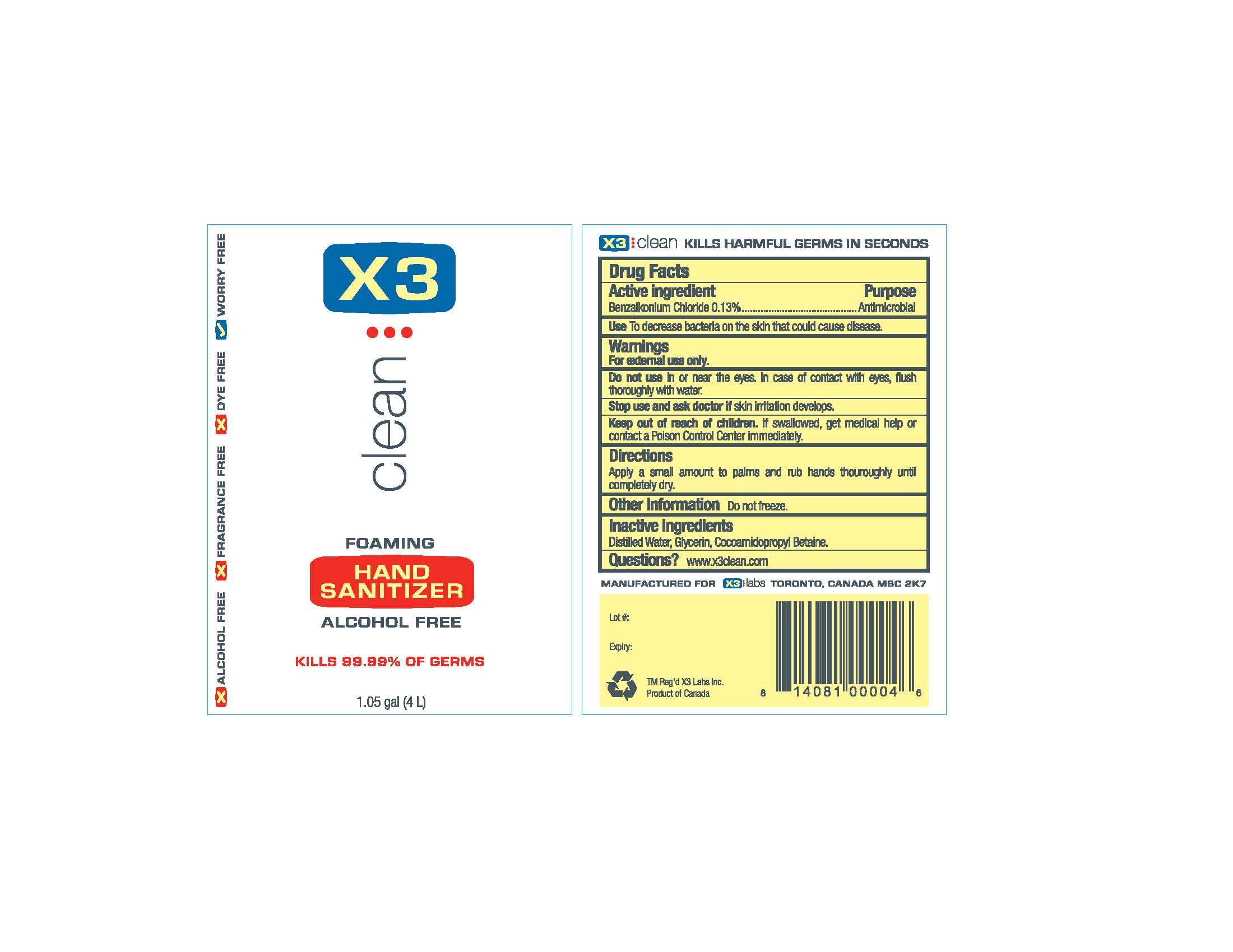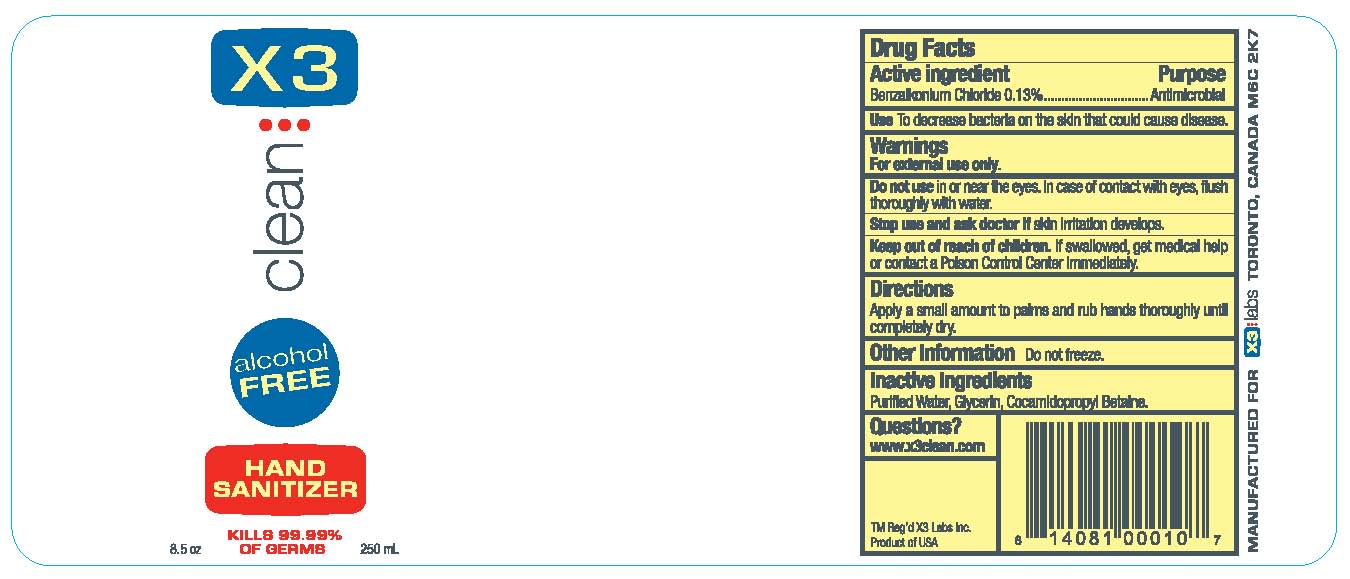 DRUG LABEL: X3 Clean
NDC: 26550-001 | Form: AEROSOL, FOAM
Manufacturer: X3 Labs Inc.
Category: otc | Type: HUMAN OTC DRUG LABEL
Date: 20250903

ACTIVE INGREDIENTS: BENZALKONIUM CHLORIDE 1.3 mg/1 mL
INACTIVE INGREDIENTS: WATER; GLYCERIN; COCAMIDOPROPYL BETAINE

X3 Hand Sanitizer (Foam)

Active Ingredient

Benzalkonium Chloride 0.13%

Purpose

Antimicrobial

Use

To decrease bacteria on the skin that could cause disease.

Warnings

For external use only. Do not use in or near eyes. In case of contact with eyes, flush thoroughly with water.

Stop use and ask doctor if skin irritation develops.

Keep out of reach of children

If swallowed, get medical help or contact a Poison Control Center immediately.

DOSAGE AND ADMINISTRATION

Directions Apply a small amount to palms and rub hands thoroughly until completely dry.

Other Information Do not freeze.

Inactive Ingredients Purified Water, Glycerin, Cocamidopropyl Betaine.

Questions? www.x3clean.com